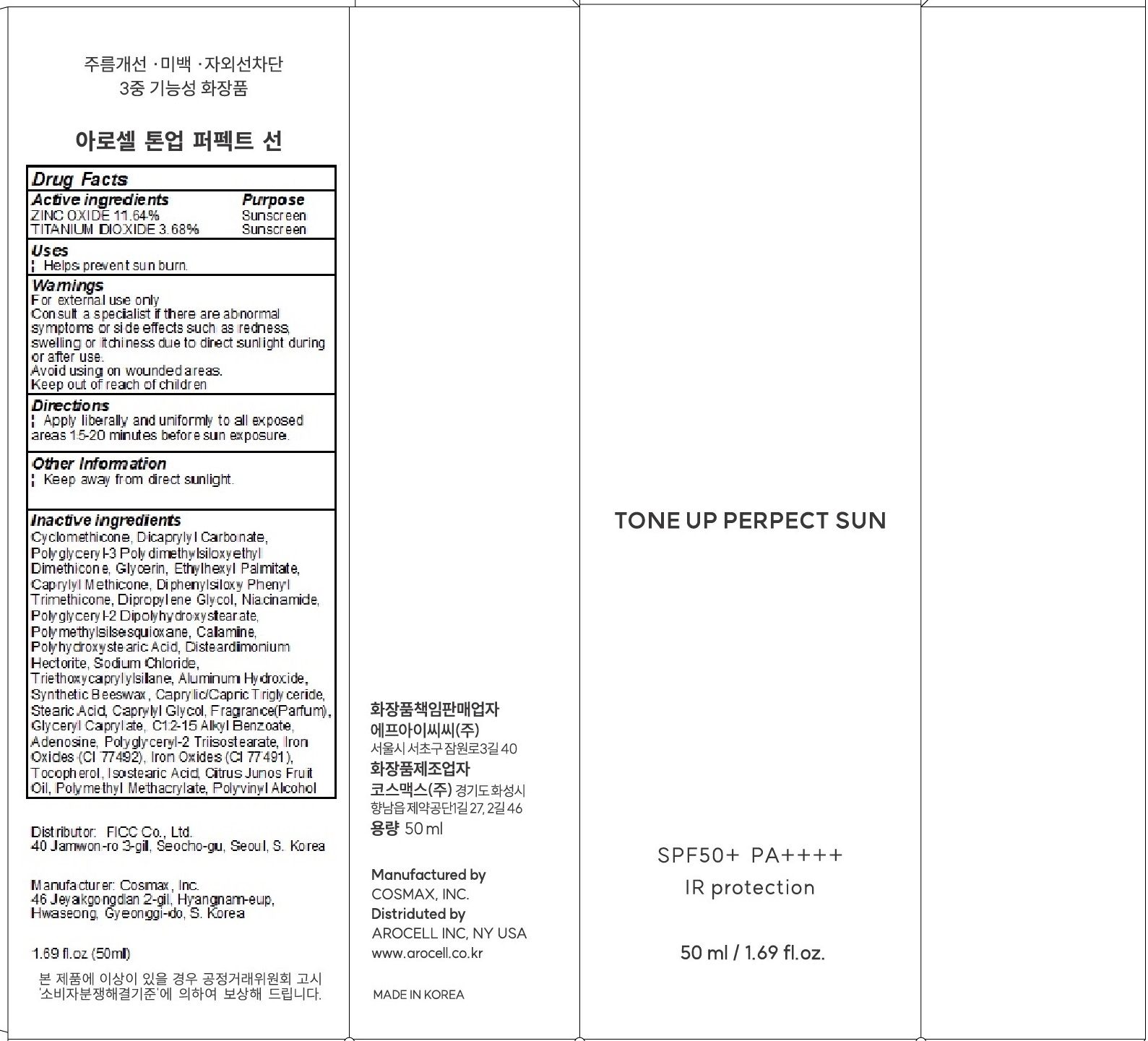 DRUG LABEL: AROCELL TONE UP PERFECT SUN
NDC: 81647-070 | Form: CREAM
Manufacturer: FICC Co., Ltd.
Category: otc | Type: HUMAN OTC DRUG LABEL
Date: 20221121

ACTIVE INGREDIENTS: ZINC OXIDE 5.82 g/50 g; TITANIUM DIOXIDE 1.84 g/50 g
INACTIVE INGREDIENTS: CYCLOMETHICONE; Dicaprylyl Carbonate; Glycerin

ACTIVE INGREDIENTS

ZINC OXIDE 11.64%
TITANIUM DIOXIDE 3.68%

INACTIVE INGREDIENTS

Cyclomethicone, Dicaprylyl Carbonate, Polyglyceryl-3 Polydimethylsiloxyethyl Dimethicone, Glycerin, Ethylhexyl Palmitate, Caprylyl Methicone, Diphenylsiloxy Phenyl Trimethicone, Dipropylene Glycol, Niacinamide, Polyglyceryl-2 Dipolyhydroxystearate, Polymethylsilsesquioxane, Calamine, Polyhydroxystearic Acid, Disteardimonium Hectorite, Sodium Chloride, Triethoxycaprylylsilane, Aluminum Hydroxide, Synthetic Beeswax, Caprylic/Capric Triglyceride, Stearic Acid, Caprylyl Glycol, Fragrance(Parfum), Glyceryl Caprylate, C12-15 Alkyl Benzoate, Adenosine, Polyglyceryl-2 Triisostearate, Iron Oxides (CI 77492), Iron Oxides (CI 77491), Tocopherol, Isostearic Acid, Citrus Junos Fruit Oil, Polymethyl Methacrylate, Polyvinyl Alcohol

PURPOSE

Sunscreen

WARNINGS

For external use only
Consult a specialist if there are abnormal symptoms or side effects such as redness, swelling or itchiness due to direct sunlight during or after use.
Avoid using on wounded areas.
Keep out of reach of children

KEEP OUT OF REACH OF CHILDREN

Uses

■ Helps prevent sun burn

Directions

■ Apply liberally and uniformly to all exposed areas 15-20 minutes before sun exposure.

Other Information

■ Keep away from direct sunlight.